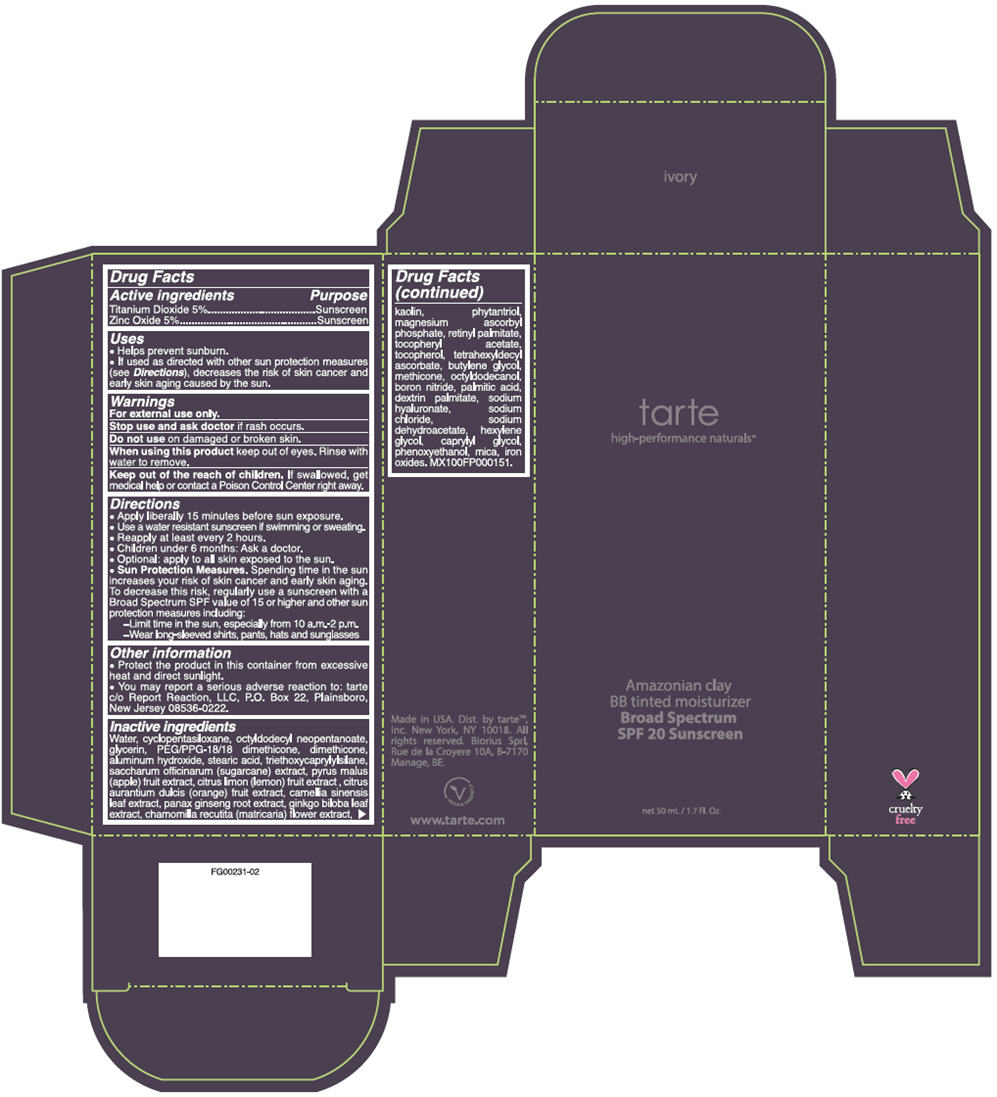 DRUG LABEL: TARTE AMAZONIAN CLAY BB TINTED MOISTURIZER BROAD SPECTRUM SPF 20 SUNSCREEN
NDC: 59735-460 | Form: CREAM
Manufacturer: MANA PRODUCT, INC.
Category: otc | Type: HUMAN OTC DRUG LABEL
Date: 20240103

ACTIVE INGREDIENTS: TITANIUM DIOXIDE 5 g/100 g; ZINC OXIDE 5 g/100 g
INACTIVE INGREDIENTS: WATER; PEG/PPG-18/18 DIMETHICONE; STEARIC ACID; PHYTANTRIOL; BUTYLENE GLYCOL; TRIETHOXYCAPRYLYLSILANE; LEMON; ORANGE; CHAMAEMELUM NOBILE FLOWER; FERROSOFERRIC OXIDE; FERRIC OXIDE RED; CAMELLIA OLEIFERA LEAF; ASIAN GINSENG; GINKGO; KAOLIN; MAGNESIUM ASCORBYL PHOSPHATE; PALMITIC ACID; HYALURONATE SODIUM; .ALPHA.-TOCOPHEROL ACETATE; TOCOPHEROL; TETRAHEXYLDECYL ASCORBATE; SUGARCANE; CYCLOMETHICONE 5; OCTYLDODECYL NEOPENTANOATE; GLYCERIN; DIMETHICONE; ALUMINUM HYDROXIDE; PHENOXYETHANOL; MICA; BORON NITRIDE; SODIUM DEHYDROACETATE; CAPRYLYL GLYCOL; SODIUM CHLORIDE; HEXYLENE GLYCOL; VITAMIN A PALMITATE; APPLE

AC BB TINTED MOISTURIZER BROAD SPECTRUM SPF 20 SUNSCREEN

ACTIVE INGREDIENTS

Titanium Dioxide 5%
Zinc Oxide 5%

PURPOSE

Sunscreen

USES

helps prevent sunburn.
If used as directed with other sun protection measures (see Directions), decreases the risk of skin cancer and early skin aging caused by the sun

WARNINGS

For external use only

Do not use on damaged or broken skin

When using this product keep out of eyes. Rinse with water to remove.

DIRECTIONS

- Apply liberally 15 minutes before sun exposure
- Use a water resistant sunscreen if swimming or sweating
- Reapply at least every 2 hours
- Children under 6 months: Ask a doctor
- Optional: apply to all skin exposed to the sun
- Sun Protection Measures. Spending time in the sun increases your risk of skin cancer and early skin aging. To decrease this risk, regularly use a sunscreen with a Broad Spectrum SPF value of 15 or higher and other sun protection measures including:
- Limit time in the sun, especially from 10 a.m.-2 p.m.
- Wear long-sleeved shirts, pants, hats and sunglasses

OTHER INFORMATION

Protect the product in this container from excessive heat and direct sunlight

INACTIVE INGREDIENTS

Water, cyclopentasiloxane, PEG/PPG-18/18 dimethicone, octyldodecyl neopentanoate, glycerin, dimethicone, aluminum hydroxide, stearic acid, phenoxyethanol, mica, boron nitride, sodium dehydroacetate, caprylyl glycol, sodium chloride, phytantriol, kaolin, magnesium ascorbyl phosphate, palmitic acid, dextrin palmitate, sodium hyaluronate, hexylene glycol, retinyl palmitate, tocopheryl acetate, tocopherol, tetrahexyldecyl ascorbate, methicone, butylene glycol, triethoxycaprylylsilane, calcium sodium phosphosilicate, saccharum officinarum (sugar cane) extract, pyrus malus (apple) fruit extract, citrus limon (lemon) fruit extract, citrus aurantium dulcis (orange) fruit extract, camellia oleifera leaf extract, panax ginseng root extract, ginkgo biloba leaf extract, anthemis nobilis flower extract, iron oxides.

Stop use and ask a doctor if rash occurs.

RECENT MAJOR CHANGES

Dosage & Admin update

Keep out of reach of children. If product is swallowed, get medical help or contact a Poison Control Center right away.